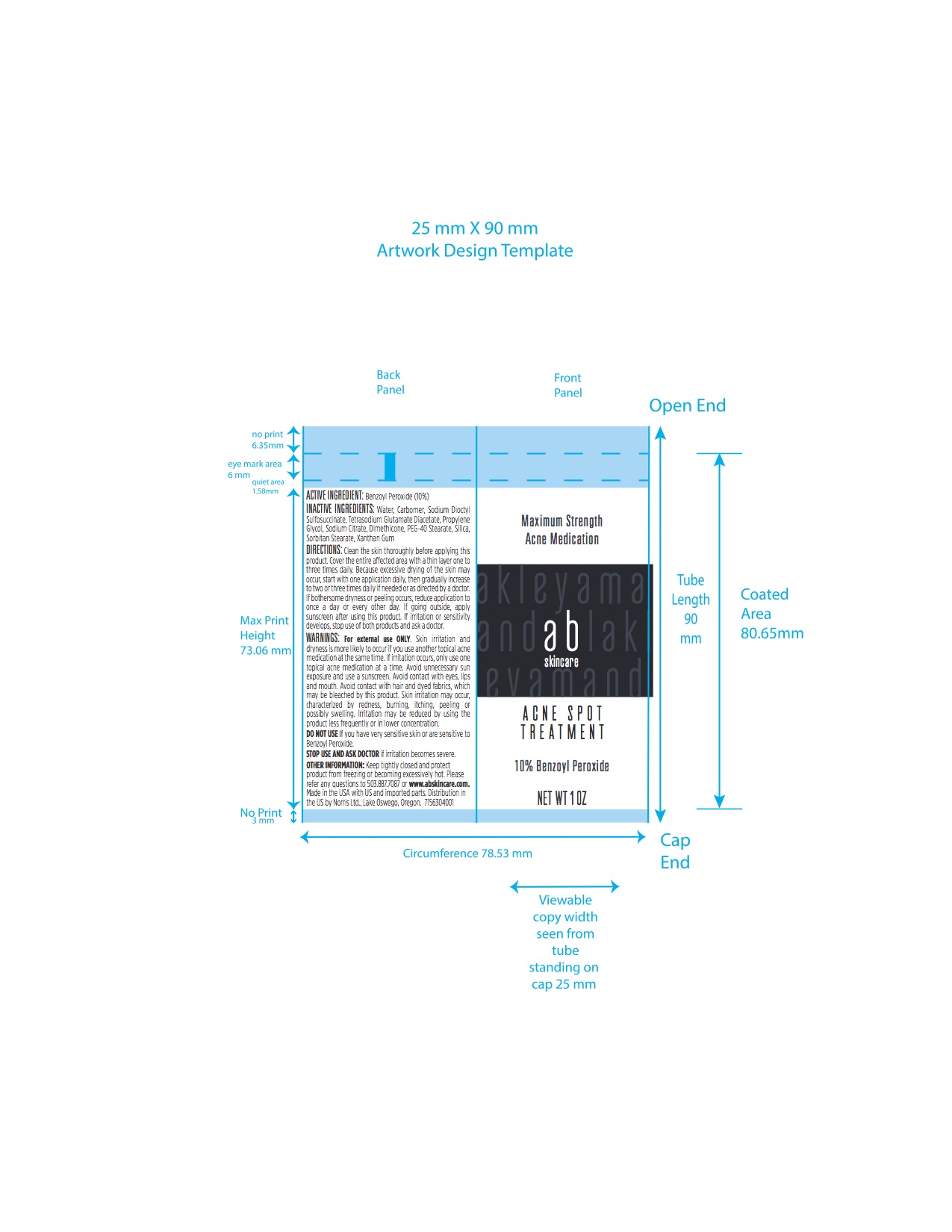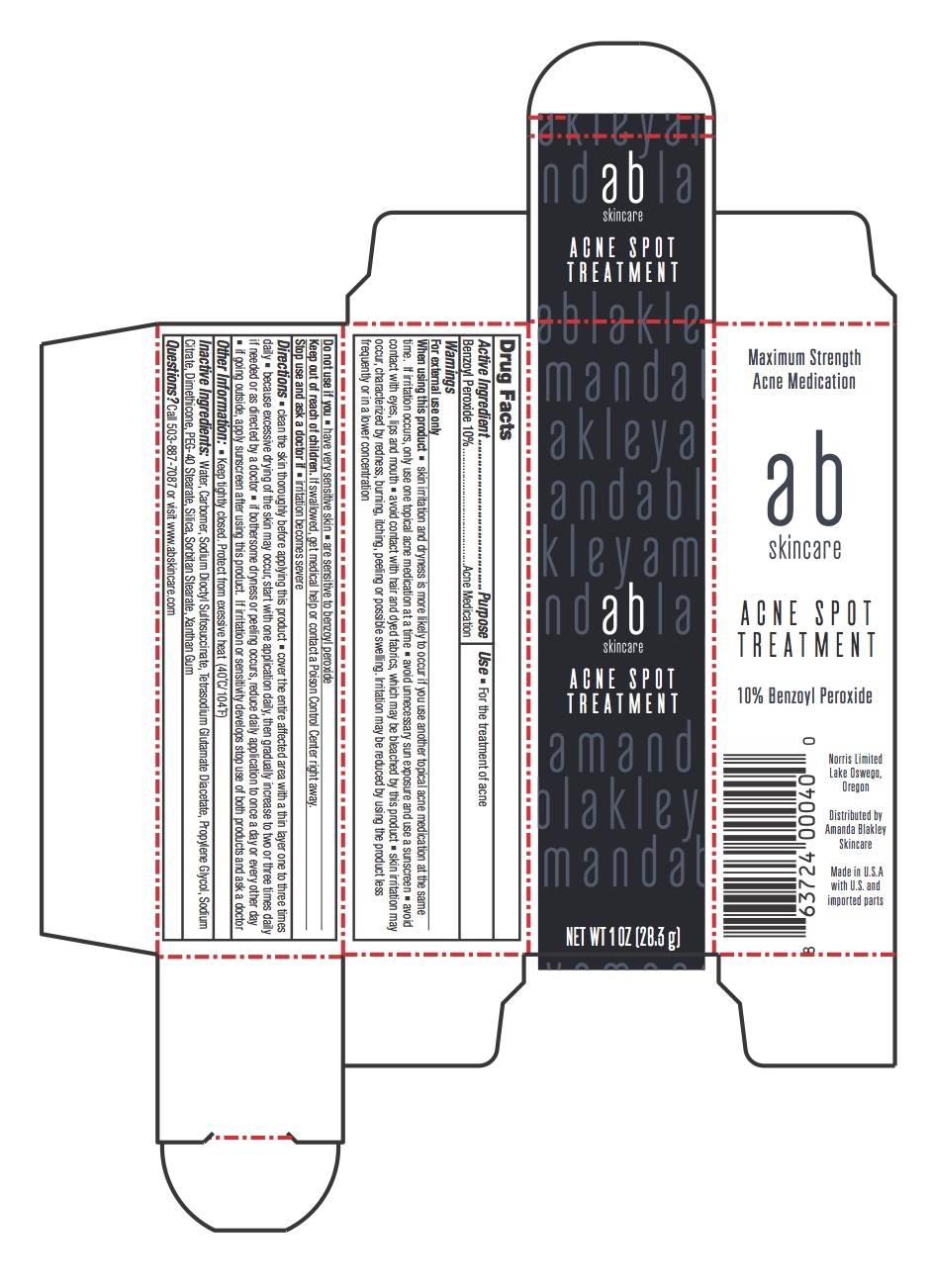 DRUG LABEL: AB Skincare Acne Spot Treatment
NDC: 71563-0400 | Form: CREAM
Manufacturer: Norris Ltd
Category: otc | Type: HUMAN OTC DRUG LABEL
Date: 20180927

ACTIVE INGREDIENTS: BENZOYL PEROXIDE 28.3 g/100 g
INACTIVE INGREDIENTS: METHOXY PEG-40; XANTHAN GUM; CARBOXYPOLYMETHYLENE; WATER; DIMETHICONE 1000; SORBITAN MONOSTEARATE; SODIUM CITRATE; DOCUSATE SODIUM; TETRASODIUM GLUTAMATE DIACETATE; 2-PHENYLPROPANAL PROPYLENE GLYCOL ACETAL

WARNINGS

For external use ONLY. Skin irritation and dryness is more likely to occur if you use another topical acne medication at the same time. If irritation occurs, only use one topical acne medication at a time. Avoid unnessary sun exposure and use a sunscreen. Avoid contact with eyes, lips and mouth. Avoid contact with hair, dyed fabrics, which may be bleached by this product. Skin irritation may occur characterized by redness, burning, itching, peeling or possibly swelling, Irritation may be reduced by using the product less frequently or in lower concentration.

DO NOT USE If you have very sensitive skin or are sensitive to Benzoyl Peroxide. STOP USE AND ASK DOCTOR if irritation becomes severe.

INSTRUCTIONS FOR USE

Clean the skin thoroughly before applying this product. Cover the entire affected area with a thin layer one to three times daily. Because excessive drying of the skin may occur, start with one application daily, then gradually increase to two or three times daily if needed or as directed by a doctor. If bothersome dryness or peeling occurs, reduce application nto once a day or every other day. If going outside, apply sunscreen after using this product. If irritation or sensitivity develops, stop use of both products and and ask a doctor.

GERIATRIC USE

Keep tightly closed and protect product from freezing or becoming excessively hot. Please refer any questions to 503.887.7087 or www.abskincare.com

DOSAGE AND ADMINISTRATION

One application daily, then gradually increase to two or three times daily if needed or as directed by a doctor. If bothersome dryness occurs, reduce daily aplication to once a day or every other day.

INACTIVE INGREDIENT

Water, carbomer, Sodium Dioctyl Sulfosuccinate, Tetrasodium Glutamate Diacetate, Propylene Glycol, Sodium Citrate, Dimethicone, PEG_40, Silica, Sorbitan Stearate, Xanthan Gum

INDICATIONS AND USAGE

If irritation or sensitivy develops stop use of both products and ask a doctor

PURPOSE

For the treatment of acne

Keep out of reach of children. If swallowed, get medical help or contact a Poison Control Center right away.

ACTIVE INGREDIENT

Benzoyll Peroxide 10%